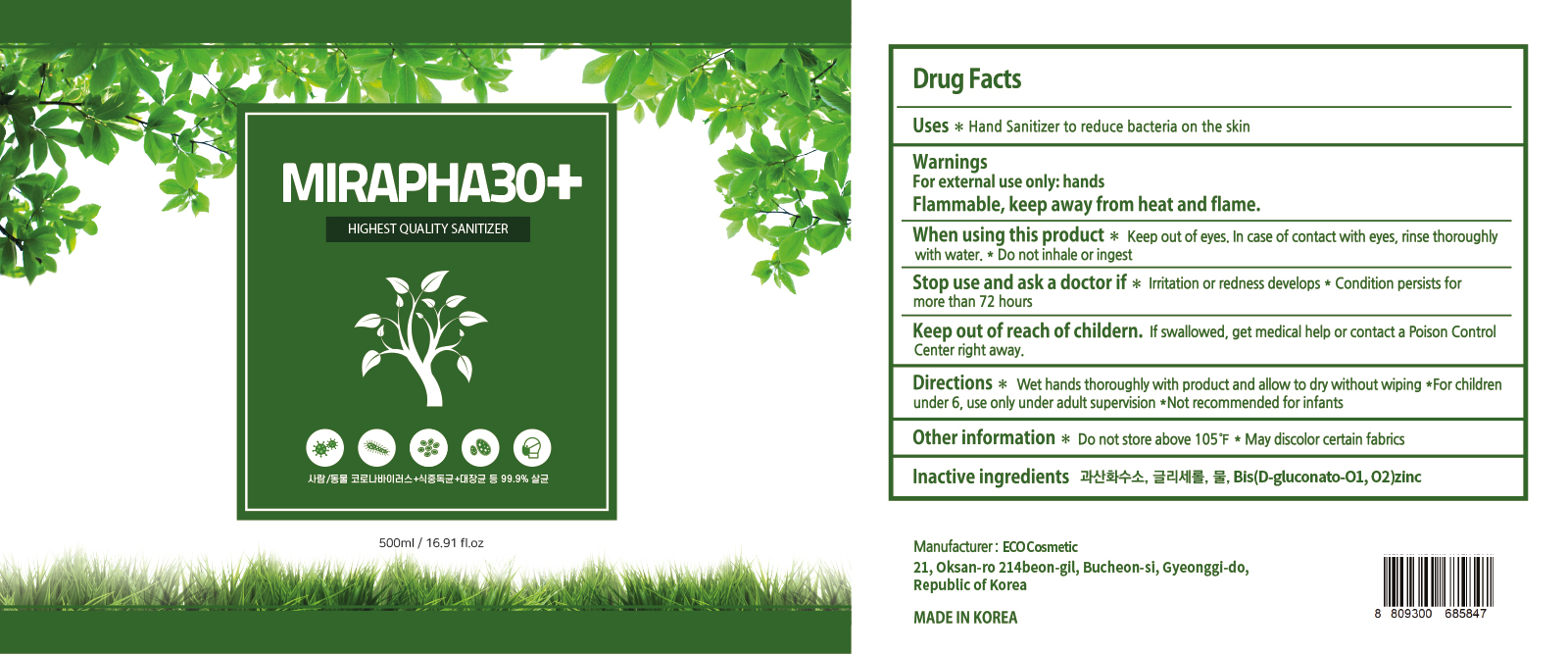 DRUG LABEL: MIRAPHA30
NDC: 78780-201 | Form: LIQUID
Manufacturer: ECOCOSMETICS
Category: otc | Type: HUMAN OTC DRUG LABEL
Date: 20200615

ACTIVE INGREDIENTS: HYDROGEN PEROXIDE 3 mL/100 mL
INACTIVE INGREDIENTS: WATER; GLYCERIN; ZINC GLUCONATE

Active ingredient

hydrogen peroxide 3%

Purpose

Antimicrobial

Uses

Hand Sanitizer to reduce bacteria on the skin

Warnings

For external use only: hands

Flammable, keep away from heat and flame.

When using this product

Keep out of eyes. In case of contact with eyes, rinse thoroughly with water. Do not inhale or ingest

Stop use and ask a doctor if

Irritation or redness develops. Condition persists for more than 72 hours

Keep out of reach of children.

If swallowed, get medical help or contact a Poison Control Center right away.

Directions

Wet hands thoroughly with product and allow to dry without wiping. For children under 6, use only under adult supervision. Not recommended for infants

Other information

Do not store above 105F. May discolor certain fabrics

Inactive ingredients

Glycerin, Water, Bis(D-gluconato-01, 02)zinc